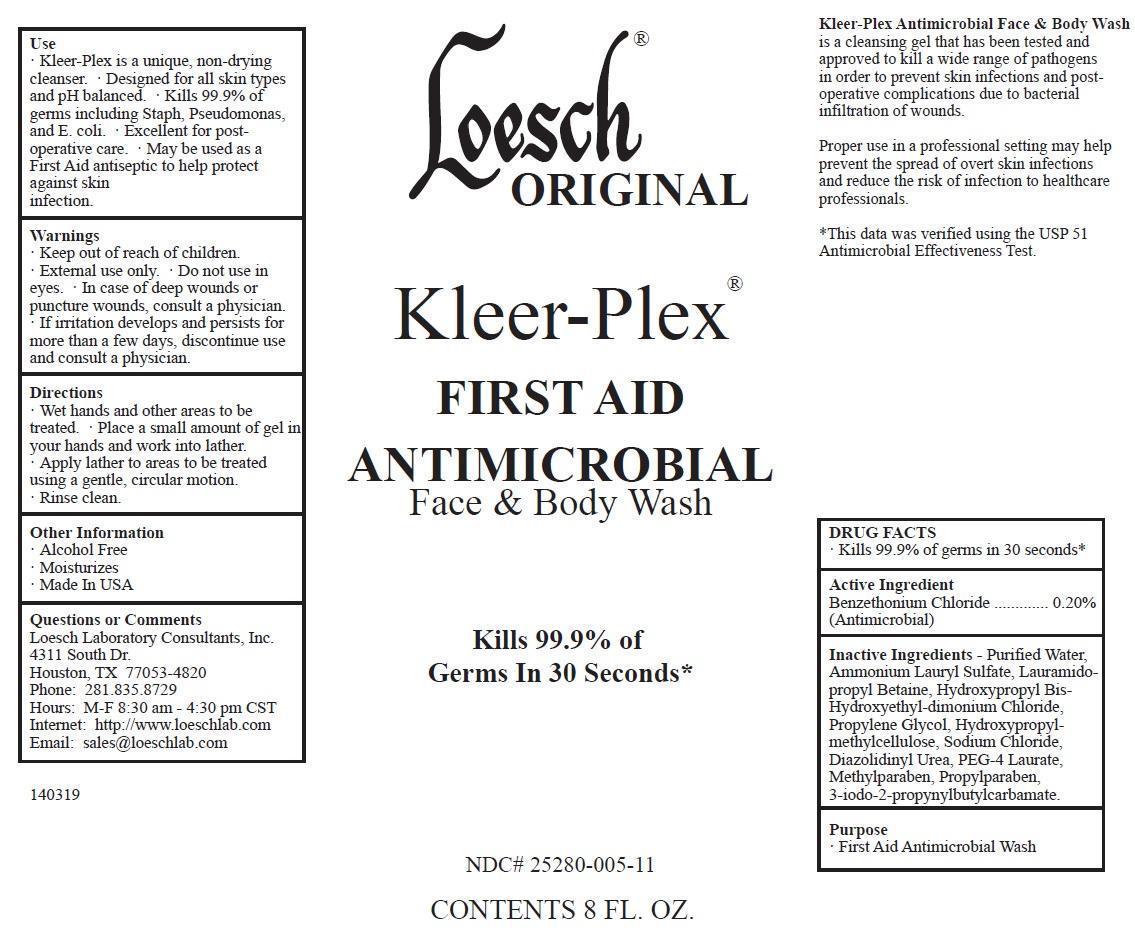 DRUG LABEL: Loesch Original Kleer-Plex
NDC: 25280-005 | Form: GEL
Manufacturer: Loesch Laboratory Consultants, Inc.
Category: otc | Type: HUMAN OTC DRUG LABEL
Date: 20140324

ACTIVE INGREDIENTS: BENZETHONIUM CHLORIDE 2 mg/1 mL
INACTIVE INGREDIENTS: WATER; AMMONIUM LAURYL SULFATE; LAURAMIDOPROPYL BETAINE; HYDROXYPROPYL BIS-HYDROXYETHYLDIMONIUM CHLORIDE; PROPYLENE GLYCOL; HYPROMELLOSES; SODIUM CHLORIDE; DIAZOLIDINYL UREA; PEG-4 LAURATE; METHYLPARABEN; PROPYLPARABEN; IODOPROPYNYL BUTYLCARBAMATE

Loesch Original Kleer-Plex Antimicrobial Face and Body Wash

DRUG FACTS

Kills 99.9% of germs in 30 seconds

-This data was verified using the USP 51 Antimicrobial Effectiveness Test

Active Ingredient

Benzethonium Chloride ............. 0.20% (Antimicrobial)

Inactive Ingredients

Purified Water, Ammonium Lauryl Sulfate, Lauramidopropyl Betaine, Hydroxypropyl Bis-Hydroxyethyldimonium Chloride, Propylene Glycol, Hydroxypropylmethylcellulose, Sodium Chloride, Diazolidinyl Urea, PEG-4 Laurate, Methylparaben, Propylparaben, 3-iodo-2-propynylbutylcarbamate.

Purpose

- First Aid Antimicrobial Wash

Use

- Kleer-Plex is a unique, non-drying cleanser.
- Designed for all skin types and pH balanced.
- Kills 99.9% of germs including Staph, Pseudomonas, and E. coli.
- Excellent for postoperative care.
- May be used as a First Aid antiseptic to help protect against skin infection.

Warnings

- Keep out of reach of children.
- External use only.
- Do not use in eyes.
- In case of deep wounds or puncture wounds, consult a physician.
- If irritation develops and persists for more than a few days, discontinue use and consult a physician.

Directions

- Wet hands and other areas to be treated.
- Place a small amount of gel in your hands and work into lather.
- Apply lather to areas to be treated using a gentle, circular motion.
- Rinse clean.

Other Information

- Alcohol Free
- Moisturizes
- Made In USA

Questions or Comments

Loesch Laboratory Consultants, Inc.
4311 South Dr.
Houston, TX 77053-4820
Phone: 281.835.8729
Hours: M-F 8:30 am - 4:30 pm CST
Internet: http://www.loeschlab.com
Email: sales@loeschlab.com

Image of Label - 8 fl. oz. - NDC# 25280-005-11

8ozLoeschKleerPlexAntimicrobialFaceBodyWash.jpg